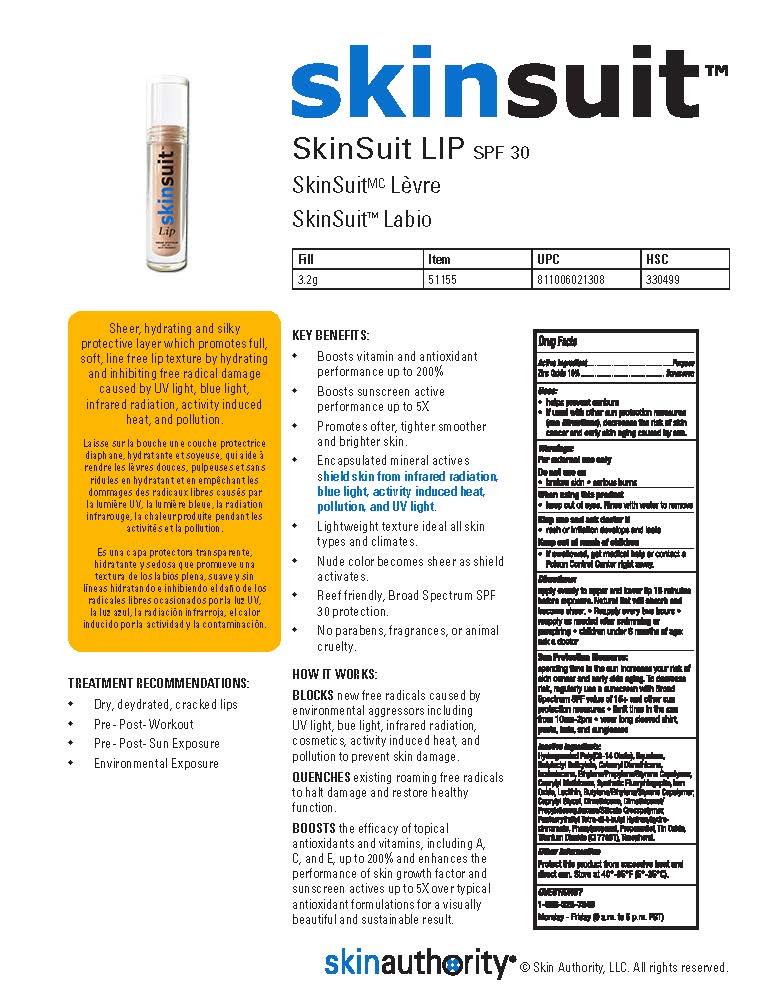 DRUG LABEL: SKINSUIT LIP
NDC: 46007-205 | Form: GEL
Manufacturer: Skin Authority LLC
Category: otc | Type: HUMAN OTC DRUG LABEL
Date: 20251218

ACTIVE INGREDIENTS: ZINC OXIDE 10 g/100 g
INACTIVE INGREDIENTS: HYDROGENATED POLY(C6-14 OLEFIN; 2 CST); SQUALANE; BUTYLOCTYL SALICYLATE; CETEARYL METHICONE (15000 MW); ISODODECANE; CAPRYLYL TRISILOXANE; SYNTHETIC WAX (1200 MW); FERRIC OXIDE RED; CAPRYLYL GLYCOL; DIMETHICONE; DIMETHICONOL/PROPYLSILSESQUIOXANE/SILICATE CROSSPOLYMER (450000000 MW); PENTAERYTHRITOL TETRAKIS(3-(3,5-DI-TERT-BUTYL-4-HYDROXYPHENYL)PROPIONATE); PHENYLPROPANOL; PROPANEDIOL; STANNIC OXIDE; TITANIUM DIOXIDE; TOCOPHEROL

Skin Authority - SKINSUIT LIP SPF-30 (46007-205)

ACTIVE INGREDIENT

ZINC OXIDE 10%

PURPOSE

SUNSCREEN

USES

- HELPS PREVENT SUNBURN
- IF USED WITH OTHER SUN PROTECTION MEASURES (SEE DIRECTIONS), DECREASES THE RISK OF SKIN CANCER AND EARLY SKIN AGING CAUSED BY SUN.

WARNINGS

FOR EXTERNAL USE ONLY.

DO NOT USE ON

- BROKEN SKIN
- SERIOUS BURNS

WHEN USING THIS PRODUCT

- KEEP OUT OF EYES. RINSE WITH WATER TO REMOVE.

STOP USE AND ASK A DOCTOR IF

- RASH OR IRRITATION DEVELOPS AND LASTS

KEEP OUT OF REACH OF CHILDREN.

- IF SWALLOWED, GET MEDICAL HELP OR CONTACT A POISON CONTROL CENTER RIGHT AWAY.

SUN PROTECTION MEASURES:

SPENDING TIME IN THE SUN INCREASES YOUR RISK OF SKIN CANCER AND EARLY SKIN AGING. TO DECREASE RISK, REGULARLY USE A SUNSCREEN WITH BROAD SPECTRUM SPF VALUE OF 15+ AND OTHER SUN PROTECTION MEASURES

- LIMIT TIME IN THE SUN FROM 10AM - 2PM
- WEAR LONG SLEEVED SHIRT, PANTS, HATS, AND SUNGLASSES

DIRECTIONS

APPLY EVENLY TO UPPER AND LOWER LIP 15 MINUTES BEFORE EXPOSURE. NATURAL TINT WILL ABSORB AND BECOME SHEER.

- REAPPLY EVERY 2 HOURS
- REAPPLY AS NEEDED AFTER SWIMMING OR PERSPIRING
- CHILDREN UNDER 6 MONTHS OF AGE: ASK A DOCTOR

INACTIVE INGREDIENT

HYDROGENATED POLY(C6-14 OLEFIN), SQUALANE, BUTYLOCTYL SALICYLATE, CETEARYL DIMETHICONE, ISODODECANE, ETHYLENE/PROPYLENE/STYRENE COPOLYMER, CAPRYLYL METHICONE, SYNTHETIC FLUORPHLOGOPITE, IRON OXIDE, LECITHIN, BUTYLENE/ETHYLENE/STYRENE COPOLYMER, CAPRYLYL GLYCOL, DIMETHICONE, DIMETHICONOL/PROPYLSILSESQUIOXANE/SILICATE CROSSPOLYMER, PENTAERYTHRITYL TETRA-DI-T-BUTYL HYDROXYHYDROCINNAMATE, PHENYLPROPANOL, PROPANEDIOL, TIN OXIDE, TITANIUM DIOXIDE (CI 77891), TOCOPHEROL.

OTHER INFORMATION

PROTECT THIS PRODUCT FROM EXCESSIVE HEAT AND DIRECT SUN. STORE AT 40° - 95°F (5° - 35°C).

QUESTIONS?

1-866-325-7546

MONDAY - FRIDAY (9 A.M. TO 5 P.M. PST)